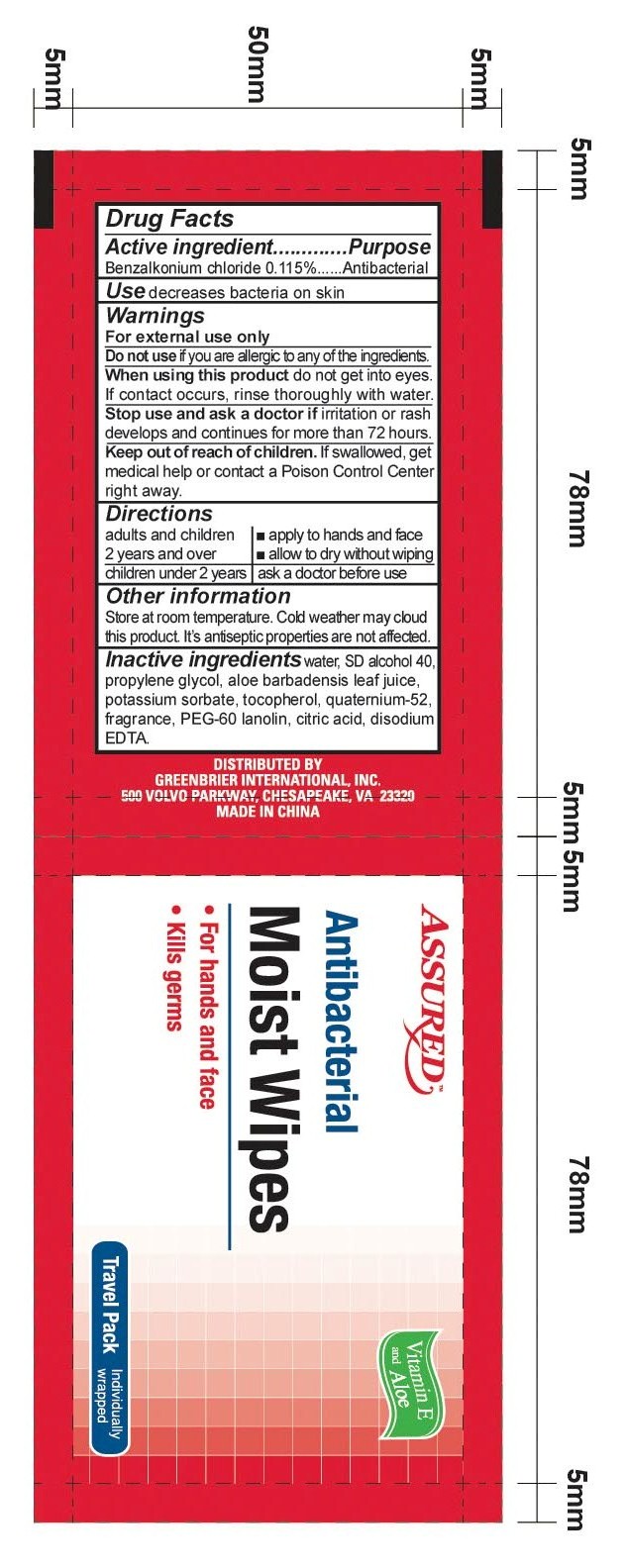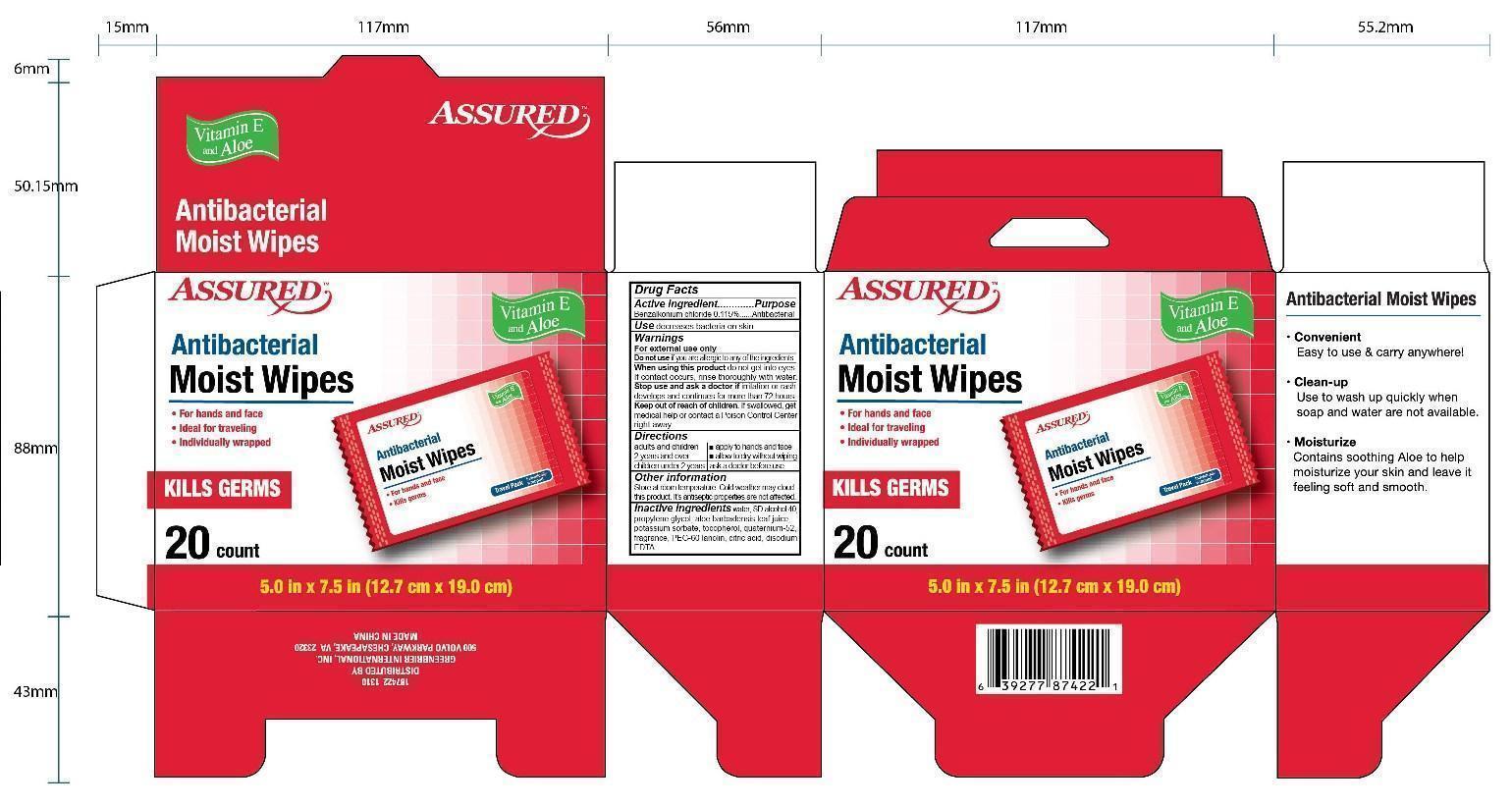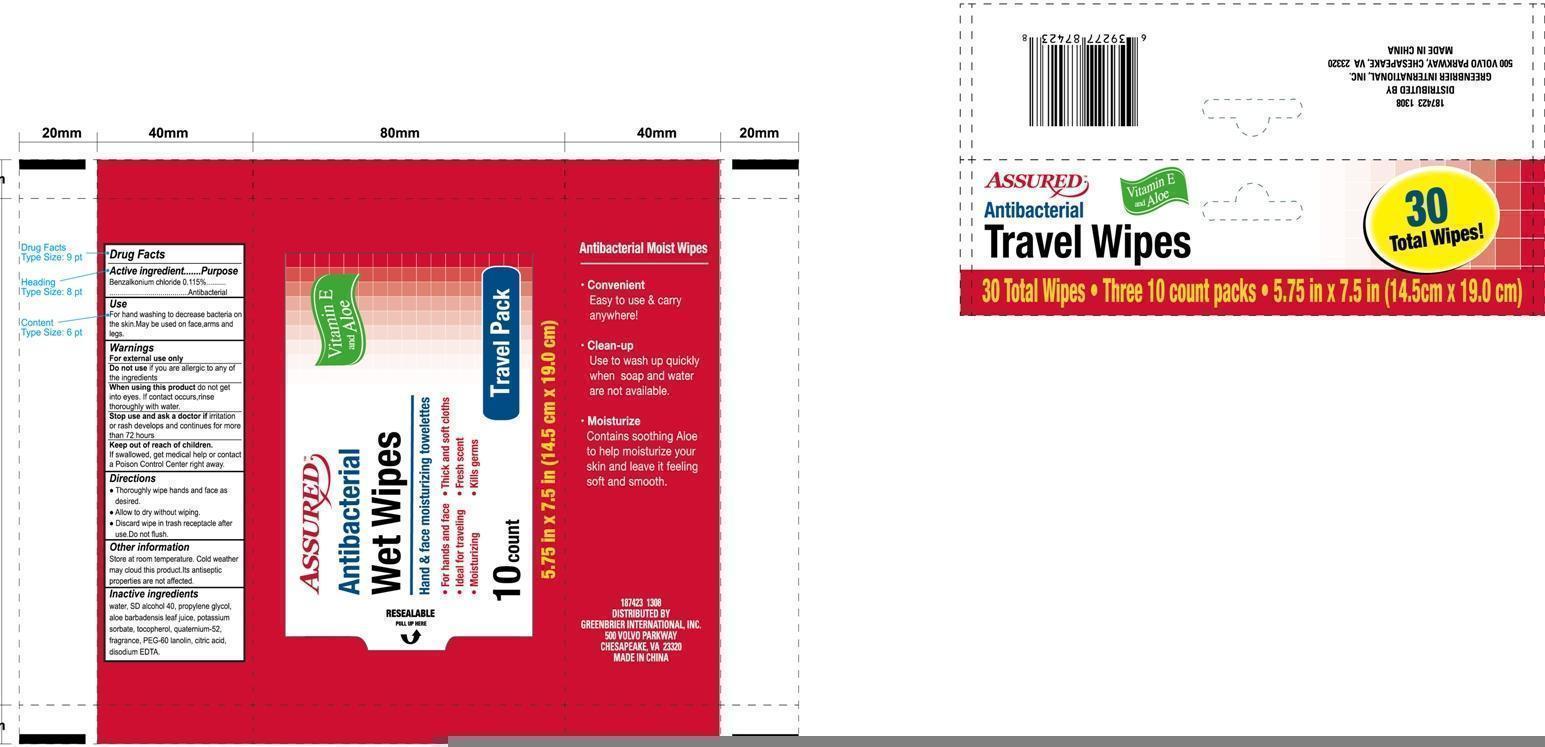 DRUG LABEL: Antibacterial Wet Wipes
NDC: 59575-501 | Form: SWAB
Manufacturer: Hebei Yihoucheng Commodity Co.,Ltd.
Category: otc | Type: HUMAN OTC DRUG LABEL
Date: 20130824

ACTIVE INGREDIENTS: BENZALKONIUM CHLORIDE 0.115 g/100 g
INACTIVE INGREDIENTS: PROPYLENE GLYCOL; ALOE VERA LEAF; ALCOHOL; POTASSIUM SORBATE; TOCOPHEROL; QUATERNIUM-22; PEG-60 CASTOR OIL; CITRACONIC ACID; DISODIUM EDTA-COPPER; Water

ASSURED ANTIBACTERIAL WET WIPES

Active ingredient

Benzalkonium chloride 0.115%

Purpose

Antibacterial

Use

decreases bacteria on skin

Warnings

For external use only.
Do not use over large areas of the body
if you are allergic to any of the ingredients.
When using this product do not get into eyes.
If contact occurs, rinse thoroughly with water.
Stop use and ask a doctor if irritation or rash
develops and continues for more than 72 hours.
Keep out of reach of children.
If swallowed, get medical help or contact
a Poison Control Center right away.

Keep out of reach of children

if swallowed
get medical help or contact a Poison Control Center right away.

Directions

For adults and children of 2 years and over use
on hands and face to clean and refresh, allow
skin to air dry.
For children under 2 years ask a doctor before use.

INACTIVE INGREDIENT

Water,SD Alcohol 40,Propylene Glycol,Aloe Barbadensis Leaf,Potassium sorbate,Tocopherol,Quaternium 52,PEG-60 Lanolin,Citric Acid,Disodium EDTA